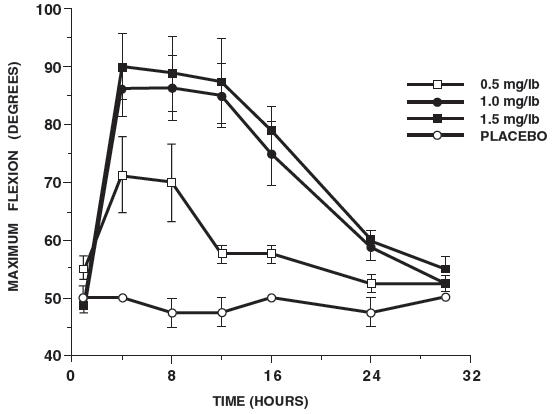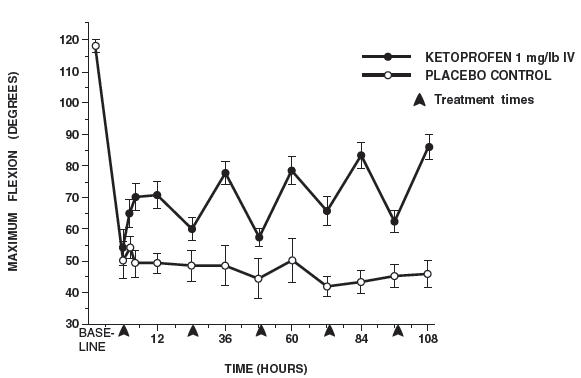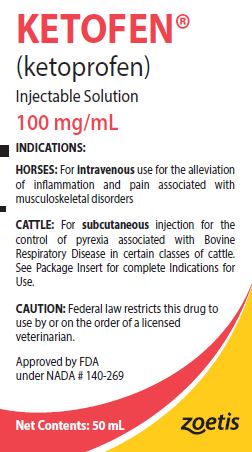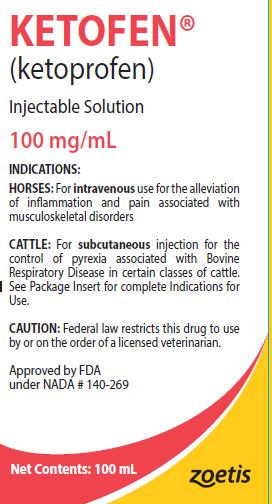 DRUG LABEL: Ketofen
NDC: 54771-4396 | Form: INJECTION, SOLUTION
Manufacturer: Zoetis Inc.
Category: animal | Type: PRESCRIPTION ANIMAL DRUG LABEL
Date: 20230331

ACTIVE INGREDIENTS: KETOPROFEN 100 mg/1 mL
INACTIVE INGREDIENTS: ARGININE 70 mg/1 mL; CITRIC ACID MONOHYDRATE; BENZYL ALCOHOL

KETOFEN®

zoetis

See other side for instructions for use in cattle.

KETOFEN®

(ketoprofen)
Injectable Solution, 100 mg/mL

For intravenous use in horses.

CAUTION

Federal law restricts this drug to use by or on the order of a licensed veterinarian.

DESCRIPTION

Ketoprofen is a non-steroidal anti-inflammatory agent of the propionic acid class that includes ibuprofen, naproxen, and fenoprofen. Active Ingredient: Each mL contains 100 mg ketoprofen/mL of aqueous solution. Inactive Ingredients: 70 mg L-Arginine/mL; citric acid (to adjust pH); benzyl alcohol, 0.025 g (as preservative).
It is packaged in a multiple dose bottle.

INDICATION

KETOFEN® (ketoprofen) is recommended for the alleviation of inflammation and pain associated with musculoskeletal disorders in the horse.

DOSAGE AND ADMINISTRATION

The recommended dosage is 1 mg/lb (1 mL/100 lbs) of body weight administered intravenously once daily. Treatment may be repeated for up to five days. Onset of activity is within two hours with peak response by 12 hours.
Use contents within 4 months of first vial puncture.

CONTRAINDICATIONS

There are no known contraindications to this drug when used as directed.

Intra-arterial injection should be avoided.

Do not use in a horse if it has previously shown hypersensitivity to ketoprofen.

USER SAFETY WARNINGS

Not for human use. Keep this and all drugs out of the reach of children.
The Safety Data Sheet (SDS) provides more detailed occupational safety information. To obtain a Safety Data Sheet contact Zoetis Inc. at 1-888-963-8471.

OTHER WARNINGS

Do not use in horses intended for human consumption.

PRECAUTIONS

As a class, cyclo-oxygenase inhibitory NSAIDs may be associated with gastrointestinal, renal, and hepatic toxicity. Sensitivity to drug-associated adverse events varies with the individual patient. Consider stopping therapy if adverse reactions, such as prolonged inappetence or abnormal feces, could be attributed to gastrointestinal toxicity. Patients at greatest risk for adverse events are those that are dehydrated, on diuretic therapy, or those with existing renal, cardiovascular, and/or hepatic dysfunction. Concurrent administration of potentially nephrotoxic drugs should be carefully approached. Since many NSAIDs possess the potential to produce gastrointestinal ulcerations and/or gastrointestinal perforation, concomitant use of ketoprofen with other anti-inflammatory drugs, such as NSAIDs or corticosteroids, should be avoided or closely monitored.
Studies to determine activity of KETOFEN when administered concomitantly with other drugs have not been conducted. Drug compatibility should be monitored closely in patients requiring
adjunctive therapy.
This product should not be used in breeding animals since the effects of KETOFEN on fertility, pregnancy or fetal health in horses have not been determined.

SIDE EFFECTS

During investigational studies, no significant side effects were reported.

CONTACT INFORMATION

For a copy of the Safety Data Sheet or to report adverse reactions, call Zoetis Inc. at 1-888-963-8471. For additional information about adverse drug experience reporting for animal drugs, contact FDA at 1-888-FDA-VETS or www.fda.gov/reportanimalae.

PHARMACOLOGY

KETOFEN is a non-narcotic, non-steroidal anti-inflammatory agent with analgesic and antipyretic properties.
In horses, intravenous dosages of ketoprofen ranging from 0.5 to 1.5 mg/lb resulted in dosage dependent anti-inflammatory effects in the chronic adjuvant carpitis model as depicted in the following graph.

MAXIMUM FLEXION (intravenous ketoprofen, mean ± sem, n = 4) [sem = standard error of the mean]

n = number of animals

Additional studies using the same model in horses have shown that the effects of ketoprofen are maximal by 12 hours and still measurable at 24 hours after each dosage as depicted in the following graph.

MAXIMUM FLEXION (mean ± sem, n = 6) [sem = standard error of the mean]

n = number of animals

TOXICITY

Horses were found to tolerate ketoprofen given intravenously at dosages of 0, 1, 3 and 5 mg/lb once daily for 15 consecutive days (up to five times the recommended dosage for three times the usual duration) with no evidence of toxic effects. In clinical studies, intravenous injection of 1 mg/lb/day for five days resulted in no injection site irritation or other side effects.
At 15-fold overdose (15 mg/lb/day) for five days one of two horses developed severe laminitis, but no gross lesions or histologic changes were observed. The toxic effects observed in the horses given a 25-fold overdose (25 mg/lb/day) for five days included inappetence, depression, icterus, abdominal swelling and postmortem findings of gastritis, nephritis and hepatitis.

HOW SUPPLIED

KETOFEN (ketoprofen) 100 mg/mL is available in 50 mL and 100 mL multidose bottles.

STORAGE CONDITIONS

Store below 25°C (77°F), with brief excursions permitted between 0°C - 40°C (32°F - 104°F).

Approved by FDA under NADA # 140-269
zoetis
Manufactured by:
Zoetis Manufacturing and Research Spain, S.L.
Girona, Spain
Distributed by:
Zoetis Inc.
Kalamazoo, MI 49007
April 2021
40029077

zoetis

See other side for instructions for use in horses.

KETOFEN®

(ketoprofen)
Injectable Solution, 100 mg/mL

For subcutaneous use in certain classes of cattle.
See INDICATIONS below.

CAUTION

Federal law restricts this drug to use by or on the order of a licensed veterinarian.

DESCRIPTION

Ketoprofen is a non-steroidal anti-inflammatory agent of the propionic acid class that includes ibuprofen, naproxen, and fenoprofen. Active Ingredient: Each mL contains 100 mg ketoprofen/mL of aqueous solution. Inactive Ingredients: 70 mg L-Arginine/mL; citric acid (to adjust pH); benzyl alcohol, 0.025 g (as preservative).
It is packaged in a multiple dose bottle.

INDICATIONS

KETOFEN® (ketoprofen) is indicated for the control of pyrexia associated with Bovine Respiratory Disease (BRD) in beef heifers, beef steers, beef calves 2 months of age and older, beef bulls, replacement dairy heifers, and dairy bulls. Not for use in reproducing animals over one year of age, dairy calves, or veal calves. Not for use in lactating dairy cattle or calves <2 months old.

DOSAGE AND ADMINISTRATION

Cattle: The recommended dosage is 3 mg/kg (1 mL/33.3 kg) or 1.36 mg/lb (1 mL/74 lb) of body weight. Treatment is administered by subcutaneous injection once daily and may be repeated for up to three days if pyrexia persists.
Use contents within 4 months of first vial puncture.
Cattle Dosing Guide:

Animal Weight (lb) | Dose Volume (mL) | Animal Weight (lb) | Dose Volume (mL)
150 | 2.1 | 600 | 8.4
200 | 2.8 | 650 | 9.1
250 | 3.5 | 700 | 9.8
300 | 4.2 | 750 | 10.5
350 | 4.9 | 800 | 11.2
400 | 5.6 | 850 | 11.9
450 | 6.3 | 900 | 12.6
500 | 7.0 | 950 | 13.3
550 | 7.7 | 1000 | 14.0

CONTRAINDICATIONS

Do not use in animals showing hypersensitivity to ketoprofen.

WITHDRAWAL PERIODS AND RESIDUE WARNINGS

Cattle must not be slaughtered for human consumption within 48-hours following last treatment with this drug product. Not for use in female dairy cattle 1 year of age or older, including dry dairy cows; use in these cattle may cause drug residues in milk and/or in calves born to these cows or heifers. Not for use in beef calves less than 2 months of age, dairy calves, and veal calves. A withdrawal period has not been established for this product in pre-ruminating calves.

USER SAFETY WARNINGS

Not for human use. Keep this and all drugs out of the reach of children.
The Safety Data Sheet (SDS) provides more detailed occupational safety information. To obtain a Safety Data Sheet contact Zoetis Inc. at 1-888-963-8471.

ANIMAL SAFETY WARNINGS

Do not use in cattle that are dehydrated or with known renal disease.

PRECAUTIONS

As a class, cyclo-oxygenase inhibitory NSAIDs may be associated with gastrointestinal, hepatic and renal toxicity. Sensitivity to drug-associated adverse effects varies with the individual patient. Patients at greatest risk for renal toxicity are those that are dehydrated, on concomitant diuretic therapy, or those with renal, cardiovascular, and/or hepatic dysfunction.
Since many NSAIDs possess the potential to induce gastrointestinal ulceration, concomitant use of KETOFEN® with other antiinflammatory drugs, such as other NSAIDs and corticosteroids, should be avoided or closely monitored. Discontinue use if fecal blood is observed.
The effects of KETOFEN® on bovine reproductive performance, pregnancy, lactation, or on animals of reproductive age intended for breeding has not been investigated.
KETOFEN® may cause injection site swelling that appears 1 to 3 days post-treatment and typically resolves by 28 days post-injection. These reactions may result in trim loss of edible tissue at slaughter.

ADVERSE REACTIONS

Repeated administration of NSAIDs can result in gastric or renal toxicity. Sensitivity to drug-associated adverse effects varies with the individual patient. Patients at greatest risk for toxicity are those that are dehydrated, on concomitant diuretic therapy, or those with pre-existing gastric ulcers, renal, cardiovascular, and/or hepatic dysfunction.

CONTACT INFORMATION

For a copy of the Safety Data Sheet or to report suspected adverse drug experiences, call Zoetis Inc. at 1-888-963-8471. For additional information about adverse drug experience reporting for animal drugs, contact FDA at 1-888-FDA-VETS or www.fda.gov/reportanimalae.

CLINICAL PHARMACOLOGY

KETOFEN is a non-narcotic, non-steroidal anti-inflammatory agent. The primary mechanism of action for ketoprofen is inhibition of the cyclooxygenase (COX) pathway leading to decreased production of prostaglandins[1]. Ketoprofen is a relatively nonselective inhibitor of the COX isozymes. After subcutaneous administration of a single dose of 3 mg/kg ketoprofen in fourteen calves, the mean and range (minimum and maximum) for the maximum plasma concentration (Cmax) was 9.40 μg/mL (7.06 – 15.8), the area under the curve to the last quantifiable point AUC(last) was 67.4 μg•h/mL (48.4 – 96.9), the time to maximum plasma concentration (Tmax) was 1.54 hours (0.67-2.0), and the half-life (t1/2) was 3.03 hours (2.48-3.88). Ketoprofen has shown linear pharmacokinetics across a 1 to 15 mg/kg dose range and has shown little to no accumulation on multiple dosing with a 24-hour dose interval.

EFFECTIVENESS

The control of pyrexia associated with bovine respiratory disease (BRD) was demonstrated in a single multisite study. Cattle exhibiting clinical signs of BRD and having a rectal temperature of at least 104.5°F were enrolled. A total of 202 cattle were administered either a single subcutaneous injection of KETOFEN® (3.0 mg/kg BW) or a single subcutaneous injection of saline (0.028 mL/kg BW) on day 0. Six hours after treatment, rectal temperatures were measured. The treatment success rate of the KETOFEN®-treated group was compared to the treatment success rate in the saline-treated group. A treatment success was defined as a decrease in rectal temperature of ≥ 2°F in an individual animal. The percent of animals with a ≥ 2 degree decrease in rectal temperature at 6 hours post-treatment was significantly different and higher (P=0.0215) in the KETOFEN® group (74.3%) vs. the saline treated group (5.9%).

TARGET ANIMAL SAFETY

Margin of Safety: KETOFEN® was injected with a 1X (3 mg/kg BW), 3X (9 mg/kg BW), and 5X (15 mg/kg BW) dose daily for 9 consecutive days (3 times the maximum recommended duration). The only treatment-associated finding present at a 1X (3 mg/kg BW) dose for 9 days was minimal to mild gross and microscopic renal tubular lesions. No ketoprofen-related changes were noted in clinical or general health observations, hematology, urinalysis, fecal occult blood, or serum chemistries in cattle administered a 1X (3 mg/kg BW) dose for 9 days. At a 3X dose, subclinical focal ulcers in the abomasum and minimal to mild renal lesions were present. Cattle injected with a 5X dose of ketoprofen for 9 days had similar treatment related findings, except for one of eight calves which had clinical signs of toxicity, due to peritonitis subsequent to abomasal ulceration on the 9th treatment day. Discontinue treatment if fecal blood is observed. Do not use in cattle that are dehydrated or with known renal disease.
Injection site safety: Eight calves were injected with a 1X dose of ketoprofen daily for 3 consecutive days with clinical observations of injection sites with necropsy on days 7, 14, 28, and 42. Injection of 3 consecutive doses of KETOFEN® resulted in transient injection site reactions palpable through 14 days, with resolution by 28 days post-administration. Injection site lesions included discoloration involving the skin and subcutaneous tissue on Day 7. By Day 42 discoloration was limited to subcutaneous tissue. Subcutaneous injection of ketoprofen can cause a transient local tissue reaction. These reactions may result in trim loss of edible tissue at slaughter.
Field safety: There were no adverse events reported in investigational field studies with the injection of KETOFEN® under the intended conditions of use.

REFERENCES

1. Paresh B, R.s., RD Varia, JH Patel, UD Patel, SK Bhavsar and AM Thaker, Impact of multiple intravenous administrations of ketoprofen on blood profile in cow calves. Inter J Vet Sci, 2012. 1(1): p. 34-36.

HOW SUPPLIED

KETOFEN® (ketoprofen) 100 mg/mL is available in 50 mL and 100 mL multidose bottles.

STORAGE CONDITIONS

Store below 25°C (77°F), with brief excursions permitted between 0°C - 40°C (32°F - 104°F).

Approved by FDA under NADA # 140-269
zoetis
Manufactured by:
Zoetis Manufacturing and Research Spain, S.L.
Girona, Spain
Distributed by:
Zoetis Inc.
Kalamazoo, MI 49007
Revised: April 2021
40029077

PRINCIPAL DISPLAY PANEL - 50 mL Bottle Label

40041163

PRINCIPAL DISPLAY PANEL - 100 mL Bottle Label

40041101